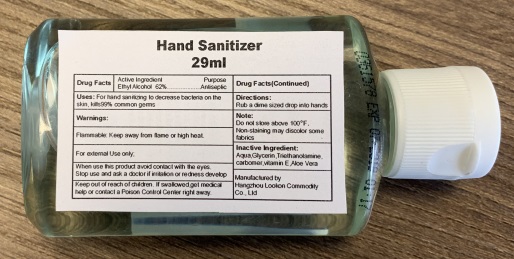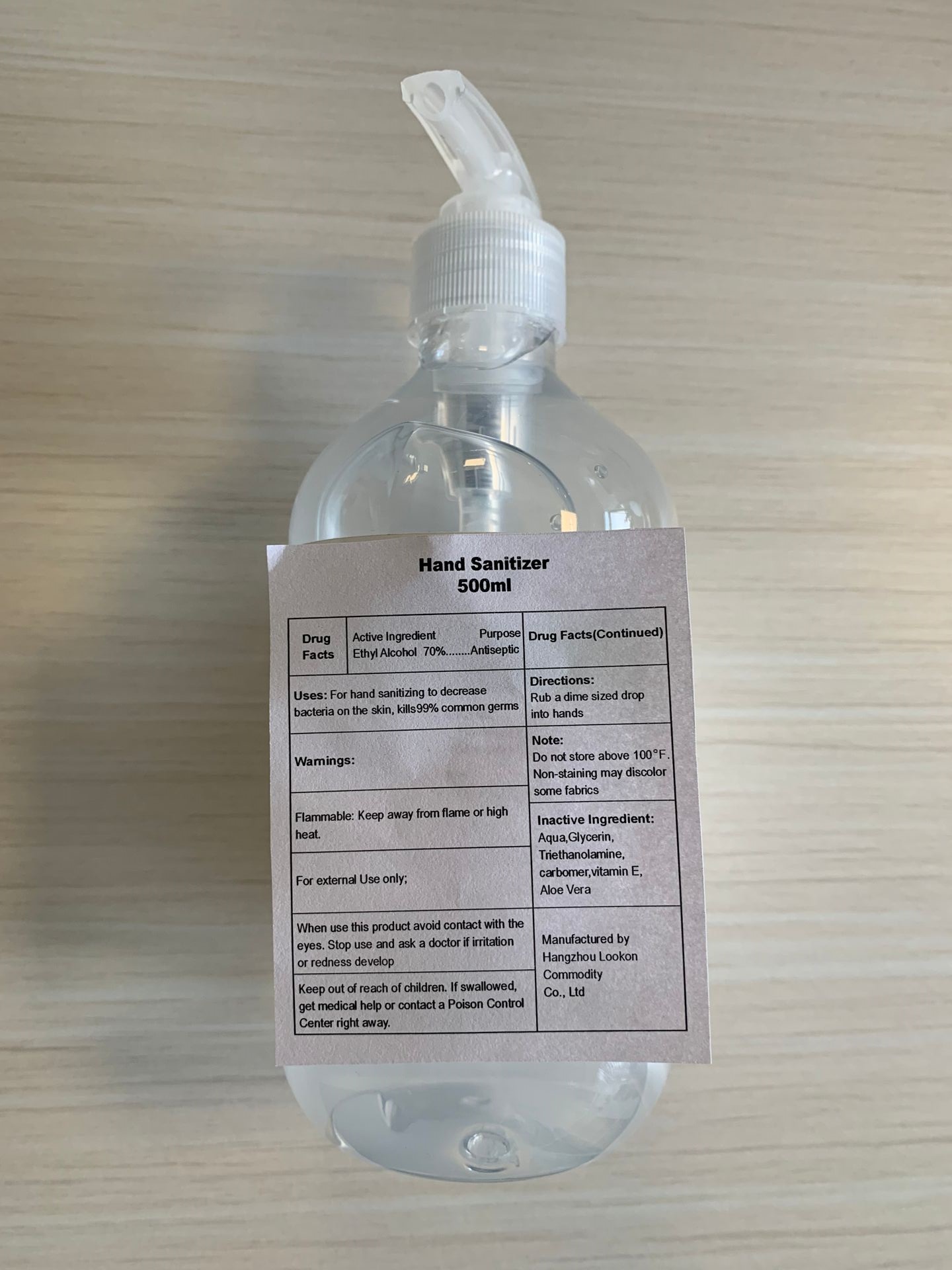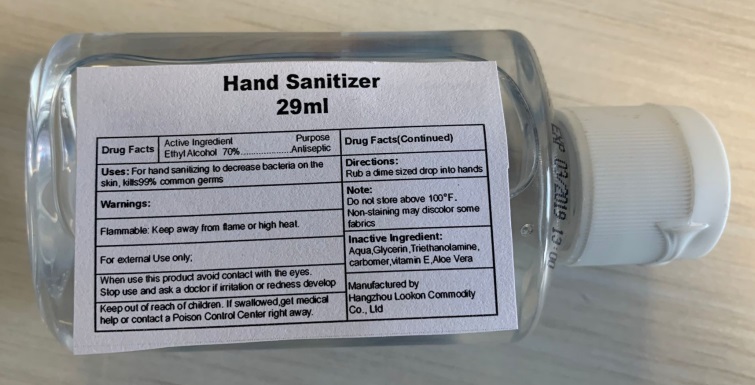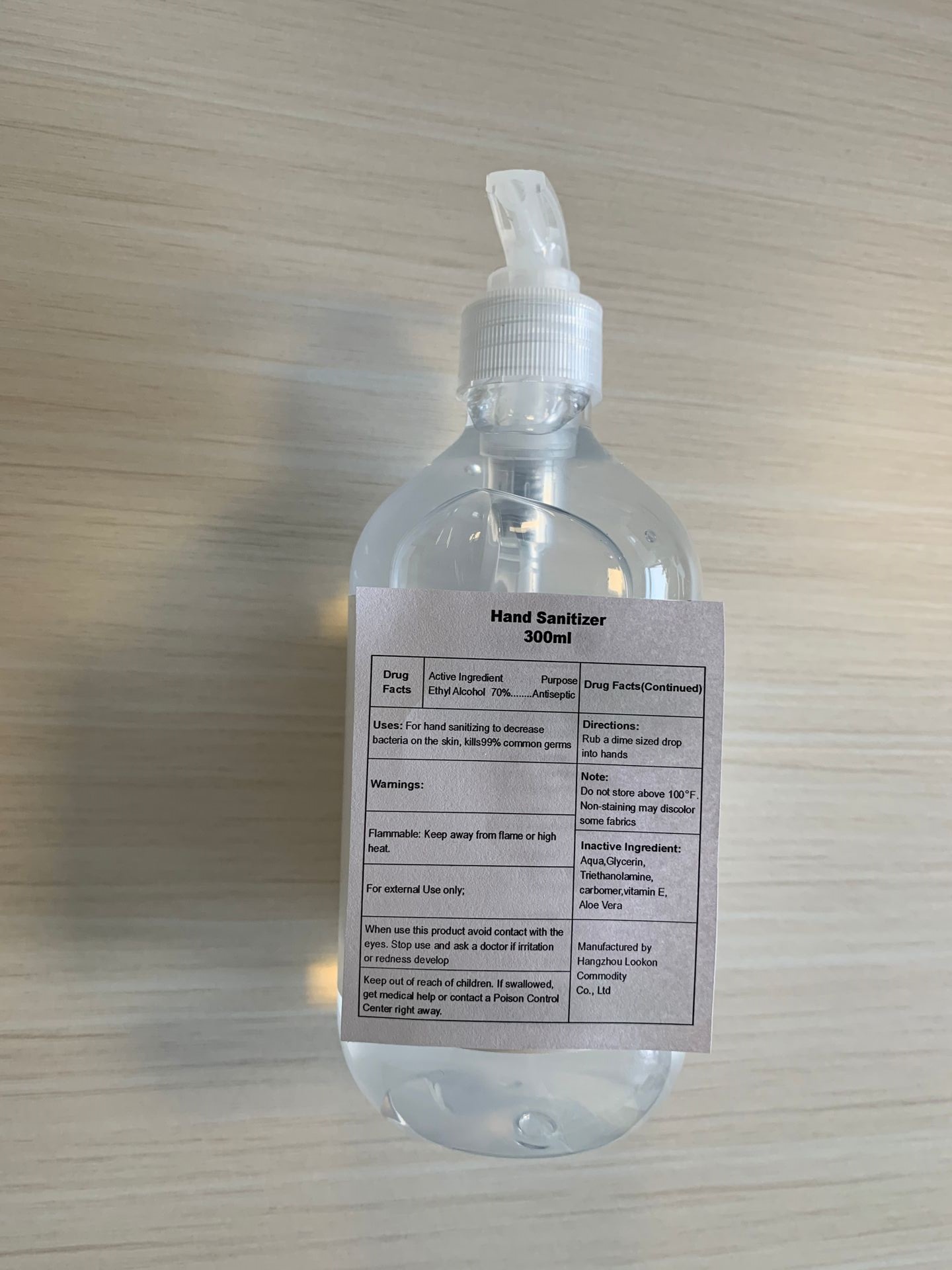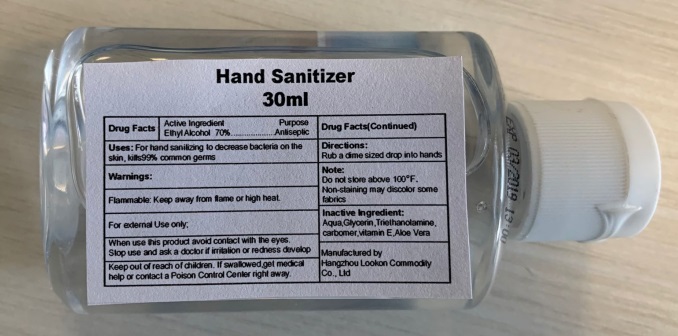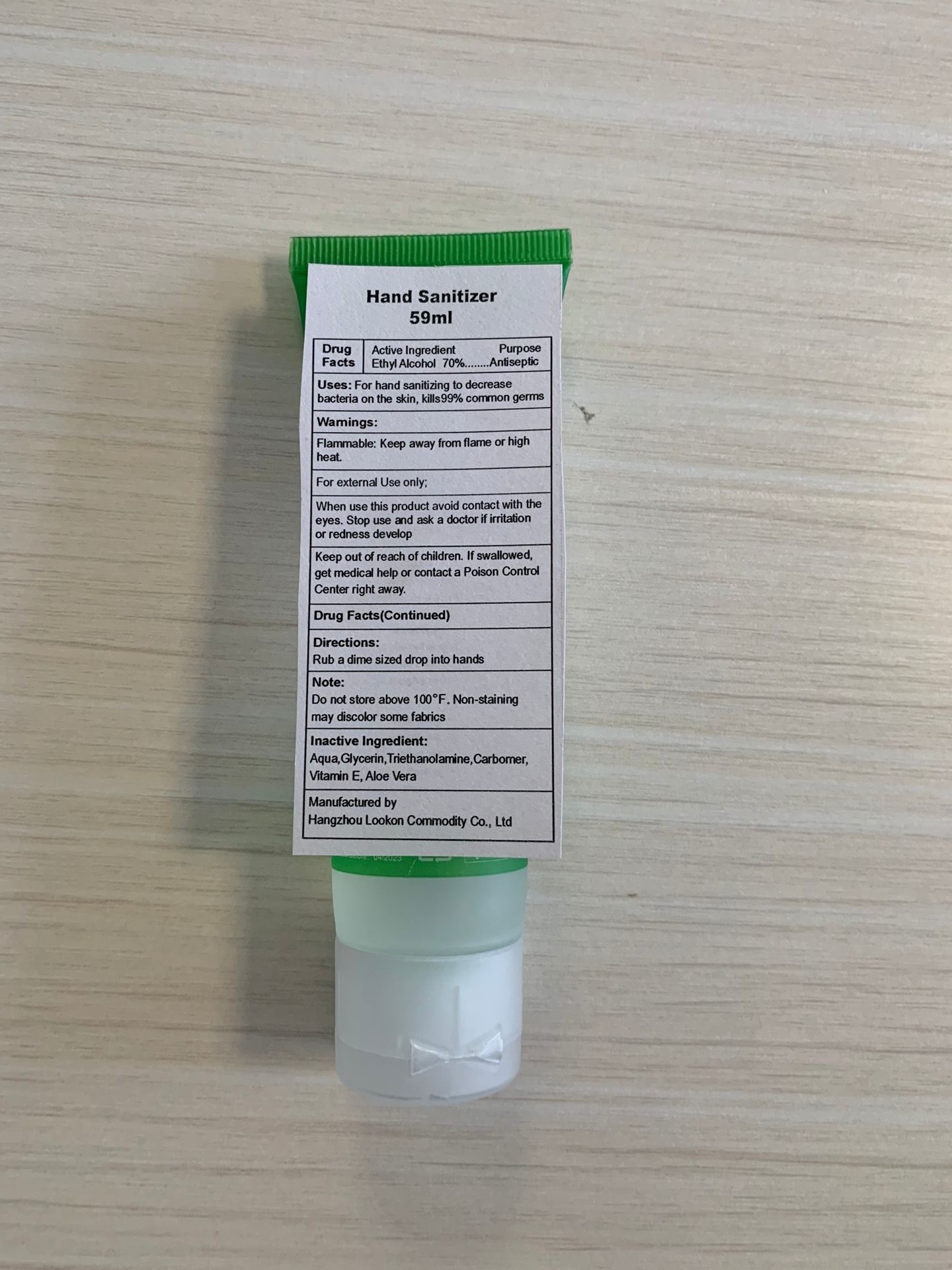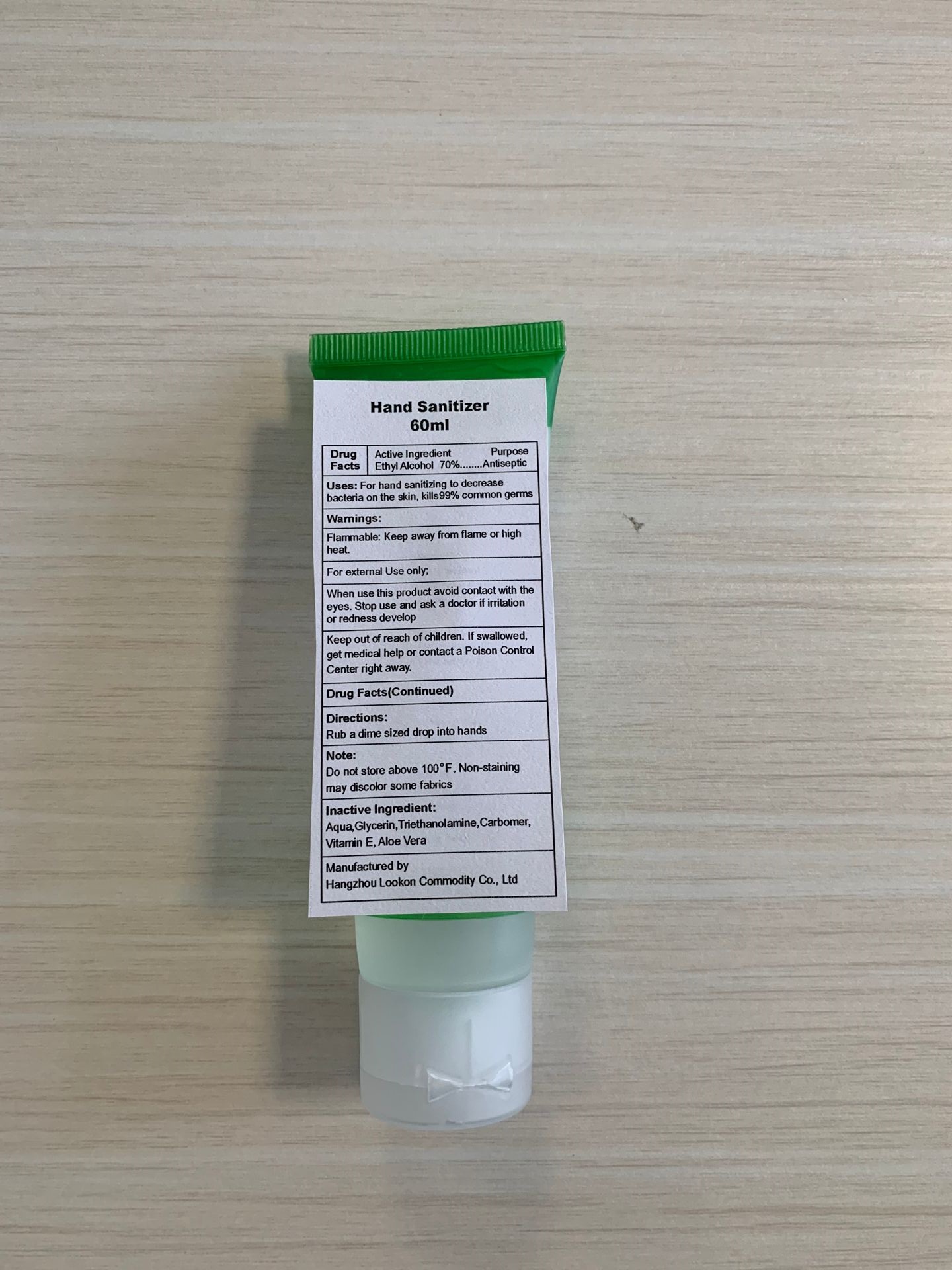 DRUG LABEL: Hand Sanitizer
NDC: 74835-002 | Form: GEL
Manufacturer: Hangzhou Lookon Commodity Co., Ltd
Category: otc | Type: HUMAN OTC DRUG LABEL
Date: 20201210

ACTIVE INGREDIENTS: ALCOHOL 62 mL/100 mL
INACTIVE INGREDIENTS: TROLAMINE; CARBOMER HOMOPOLYMER, UNSPECIFIED TYPE; ALOE VERA LEAF; .ALPHA.-TOCOPHEROL ACETATE, D-; GLYCERIN; WATER

Hand Sanitizer

Active Ingredient

Ethyl Alcohol 70%

Active Ingredient

Ethyl Alcohol 62%

Purpose

Antiseptic

Uses

For hand sanitizing to decrease bacteria on the skin, kills99% common germs

Warnings

Flammable: Keep away from flame or high heat.

For external Use only;

When use this product avoid contact with the eyes.

Stop use

Stop use and ask a doctor if irritation or redness develop

Keep out of reach of children. If swallowed,get medical help or contact a Poison Control Center right away.

Directions

Rub a dime sized drop into hands

Inactive Ingredient

Aqua,Glycerin,Triethanolamine ,carbomer,vitamin E,Aloe Vera

Package Label

Hand Sanitizer

29ml

NDC: 74835-001-01

Package Label

Hand Sanitizer

30ml

NDC: 74835-001-02

Package Label

Hand Sanitizer

59ml

NDC: 74835-001-03

Package Label

Hand Sanitizer

60ml

NDC: 74835-001-04

Package Label

Hand Sanitizer

300ml

NDC: 74835-001-05

Package Label

Hand Sanitizer

500ml

NDC: 74835-001-06

Package Label

Hand Sanitizer

29ml

NDC: 74835-002-01